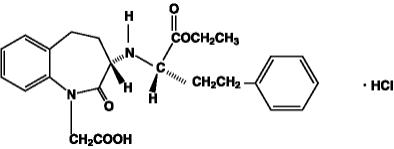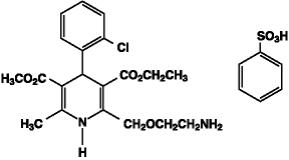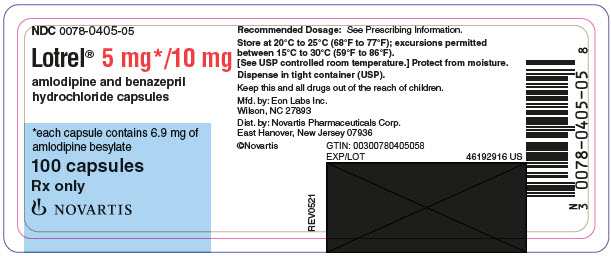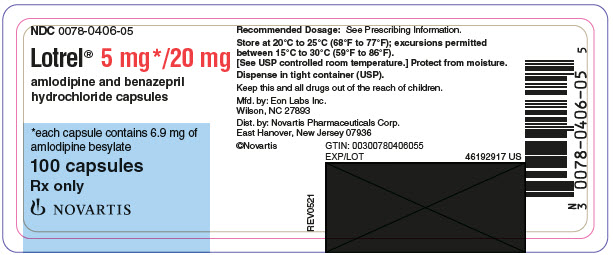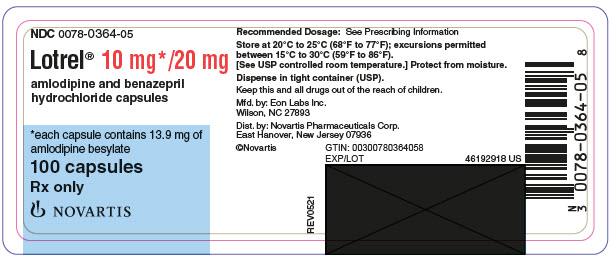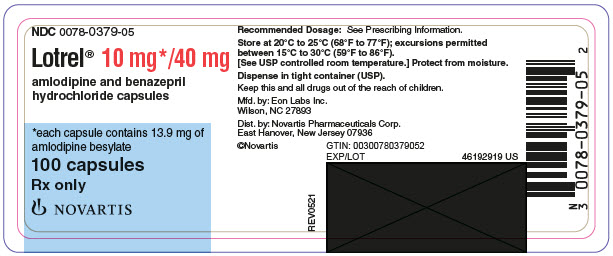 DRUG LABEL: Lotrel
NDC: 0078-0405 | Form: CAPSULE
Manufacturer: Novartis Pharmaceuticals Corporation
Category: prescription | Type: HUMAN PRESCRIPTION DRUG LABEL
Date: 20230801

ACTIVE INGREDIENTS: AMLODIPINE BESYLATE 5 mg/1 1; BENAZEPRIL HYDROCHLORIDE 10 mg/1 1
INACTIVE INGREDIENTS: CALCIUM PHOSPHATE, UNSPECIFIED FORM; HYPROMELLOSE, UNSPECIFIED; SILICON DIOXIDE; CROSPOVIDONE (120 .MU.M); GELATIN, UNSPECIFIED; HYDROGENATED CASTOR OIL; FERRIC OXIDE RED; LACTOSE, UNSPECIFIED FORM; MAGNESIUM STEARATE; POLYSORBATE 80; SODIUM LAURYL SULFATE; TALC; TITANIUM DIOXIDE; SODIUM STARCH GLYCOLATE TYPE A POTATO; STARCH, CORN

HIGHLIGHTS OF PRESCRIBING INFORMATION

These highlights do not include all the information needed to use LOTREL safely and effectively. See full prescribing information for LOTREL.
LOTREL (amlodipine and benazepril hydrochloride) capsules, for oral use
Initial U.S. Approval: 1995

WARNING: FETAL TOXICITY

See full prescribing information for complete boxed warning.

When pregnancy is detected, discontinue Lotrel as soon as possible (5.1).
Drugs that act directly on the renin-angiotensin system (RAS) can cause injury and death to the developing fetus (5.1).

1 INDICATIONS AND USAGE

Lotrel is a combination capsule of amlodipine, a dihydropyridine calcium channel blocker (DHP CCB) and benazepril, an angiotensin-converting enzyme (ACE) inhibitor. Lotrel is indicated for the treatment of hypertension in patients not adequately controlled on monotherapy with either agent. (1)

2 DOSAGE AND ADMINISTRATION

- Usual starting dose is 2.5/10 mg. (2.1)
- May be used as add-on therapy for patients not adequately controlled with either a dihydropyridine calcium channel blocker or an ACE inhibitor (2.2)
- Patients who experience edema with amlodipine may be switched to Lotrel containing a lower dose of amlodipine. (2.1)

3 DOSAGE FORMS AND STRENGTHS

Capsules (amlodipine/benazepril hydrochloride mg): 5/10, 5/20, 10/20, 10/40 (3)

4 CONTRAINDICATIONS

4. Do not coadminister aliskiren with ACE inhibitors, including Lotrel, in patients with diabetes. (4)
5. Lotrel is contraindicated in patients with a history of angioedema or patients who are hypersensitive to benazepril or to amlodipine. (4)
6. Lotrel is contraindicated in combination with a neprilysin inhibitor (e.g., sacubitril). Do not administer Lotrel within 36 hours of switching to or from a neprilysin inhibitor, e.g., sacubitril/valsartan. (4)

5 WARNINGS AND PRECAUTIONS

- Anaphylactoid reactions, including angioedema (5.2)
- Myocardial infarction or increased angina in patients with obstructive coronary artery disease. (5.3)
- Assess for hypotension and hyperkalemia. (5.4, 5.6)
- Titrate slowly in patients with impaired hepatic or severely impaired renal function. (5.5, 5.7)

6 ADVERSE REACTIONS

Discontinuation because of adverse reactions occurred in 4% of Lotrel-treated patients and 3% of placebo-treated patients. The most common reasons for discontinuation of therapy with Lotrel were cough and edema. (6.1)

To report SUSPECTED ADVERSE REACTIONS, contact Novartis Pharmaceuticals Corporation at 1-888-669-6682 or FDA at 1-800-FDA-1088 or www.fda.gov/medwatch.

7 DRUG INTERACTIONS

- Potassium supplements/potassium-sparing diuretics: hyperkalemia (7.1)
- Lithium: Increased serum lithium levels; toxicity symptoms (7.1)
- Injectable gold: facial flushing, nausea, vomiting, hypotension (7.1)
- Nonsteroidal Anti-Inflammatory Drugs (NSAIDs): Risk of renal dysfunction, loss of antihypertensive effect (7.1)
- Do not exceed doses greater than 20 mg daily of simvastatin (7.1)
- mTOR inhibitors: increased risk of angioedema (7.1)
- Dual inhibition of the RAS: Increased risk of renal impairment, hypotension, and hyperkalemia (7.1)
- Neprilysin inhibitors: increased risk of angioedema (7.1)

FULL PRESCRIBING INFORMATION

WARNING: FETAL TOXICITY

When pregnancy is detected, discontinue Lotrel as soon as possible (5.1).

Drugs that act directly on the renin-angiotensin system (RAS) can cause injury and death to the developing fetus (5.1).

1 INDICATIONS AND USAGE

1.1 Hypertension

Lotrel is indicated for the treatment of hypertension in patients not adequately controlled on monotherapy with either agent.

2 DOSAGE AND ADMINISTRATION

2.1 General Considerations

The recommended initial dose is amlodipine 2.5 mg/benazepril 10 mg orally once-daily.

Begin therapy with Lotrel only after a patient has either (a) failed to achieve the desired antihypertensive effect with amlodipine or benazepril monotherapy, or (b) demonstrated inability to achieve adequate antihypertensive effect with amlodipine therapy without developing edema.

The antihypertensive effect of Lotrel is largely attained within 2 weeks. If blood pressure remains uncontrolled, the dose may be titrated up to amlodipine 10 mg/benazepril 40 mg once-daily. The dosing should be individualized and adjusted according to the patient’s clinical response.

In clinical trials of amlodipine/benazepril combination therapy using amlodipine doses of 2.5 to 10 mg and benazepril doses of 10 to 40 mg, the antihypertensive effects increased with increasing dose of amlodipine in all patient groups, and the effects increased with increasing dose of benazepril in nonblack groups.

2.2 Replacement Therapy

Lotrel may be substituted for the titrated components.

3 DOSAGE FORMS AND STRENGTHS

Lotrel (amlodipine/benazepril hydrochloride) capsules are available as follows:

5/10 mg, 5/20 mg, 10/20 mg, and 10/40 mg.

4 CONTRAINDICATIONS

1. Do not coadminister aliskiren with angiotensin receptor blockers (ARBs), angiotensin-converting enzyme (ACE) inhibitors, including Lotrel in patients with diabetes.
2. Lotrel is contraindicated in patients with a history of angioedema, with or without previous ACE inhibitor treatment, or patients who are hypersensitive to benazepril, to any other ACE inhibitor, to amlodipine, or to any of the excipients of Lotrel.
3. Lotrel is contraindicated in combination with a neprilysin inhibitor (e.g., sacubitril). Do not administer Lotrel within 36 hours of switching to or from a neprilysin inhibitor, e.g., sacubitril/valsartan [see Warnings and Precautions (5.1)].

5 WARNINGS AND PRECAUTIONS

5.1 Fetal Toxicity

Lotrel can cause fetal harm when administered to a pregnant woman. Use of drugs that act on the renin-angiotensin system during the second and third trimesters of pregnancy reduces fetal renal function and increases fetal and neonatal morbidity and death. Resulting oligohydramnios can be associated with fetal lung hypoplasia and skeletal deformations. Potential neonatal adverse effects include skull hypoplasia, anuria, hypotension, renal failure, and death. When pregnancy is detected, discontinue Lotrel as soon as possible [see Use in Specific Populations (8.1)].

5.2 Angioedema and Anaphylactoid Reactions

Head and Neck Angioedema: Angioedema of the face, extremities, lips, tongue, glottis, and larynx has been reported in patients treated with benazepril. This may occur at any time during treatment. Angioedema associated with edema of the larynx, tongue, or glottis can compromise the airway and be fatal. If laryngeal stridor or angioedema of the face, tongue, or glottis occurs, discontinue treatment with Lotrel and treat immediately. When involvement of the tongue, glottis, or larynx appears likely to cause airway obstruction, appropriate therapy, e.g., administer subcutaneous epinephrine injection 1:1000 (0.3 to 0.5 mL), promptly [see Adverse Reactions (6)].

Patients with a history of angioedema may be at increased risk for angioedema while receiving Lotrel. Black patients receiving ACE inhibitors have a higher incidence of angioedema compared to nonblacks.

Patients receiving coadministration of ACE inhibitor and mTOR (mammalian target of rapamycin) inhibitor (e.g., temsirolimus, sirolimus, everolimus) therapy or a neprilysin inhibitor may be at increased risk for angioedema [see Drug Interactions (7)].

Intestinal Angioedema: Intestinal angioedema has been reported in patients treated with ACE inhibitors. These patients presented with abdominal pain (with or without nausea or vomiting); in some cases there was no prior history of facial angioedema and C-1 esterase levels were normal. The angioedema was diagnosed by procedures including abdominal CT scan or ultrasound, or at surgery, and symptoms resolved after stopping the ACE inhibitor. Intestinal angioedema should be included in the differential diagnosis of patients on ACE inhibitors presenting with abdominal pain.

Anaphylactoid Reactions During Desensitization: Two patients undergoing desensitizing treatment with hymenoptera (wasp sting) venom while receiving ACE inhibitors sustained life-threatening anaphylactoid reactions.

Anaphylactoid Reactions During Membrane Exposure: Anaphylactoid reactions have been reported in patients dialyzed with high-flux membranes and treated concomitantly with an ACE inhibitor. Anaphylactoid reactions have also been reported in patients undergoing low-density lipoprotein apheresis with dextran sulfate absorption.

5.3 Increased Angina and/or Myocardial Infarction

Worsening angina and acute myocardial infarction can develop after starting or increasing the dose of amlodipine, particularly in patients with severe obstructive coronary artery disease.

5.4 Hypotension

Lotrel can cause symptomatic hypotension, sometimes complicated by oliguria, progressive azotemia, acute renal failure, or death. Symptomatic hypotension is most likely to occur in patients who have heart failure, severe aortic or mitral stenosis, obstructive hypertrophic cardiomyopathy or have been volume or salt depleted as a result of diuretic therapy, dietary salt restriction, dialysis, diarrhea, or vomiting. Correct volume and salt depletion before starting therapy with benazepril. If hypotension occurs, place the patient in the supine position and give physiological saline intravenously if needed. Continue treatment with benazepril once blood pressure and volume have returned to normal.

In patients with congestive heart failure, start Lotrel therapy under close medical supervision; follow closely for the first 2 weeks of treatment and whenever the dose of the benazepril component is increased or a diuretic is added or its dose increased.

In patients undergoing surgery or during anesthesia with agents that produce hypotension, benazepril will block the angiotensin II formation that could otherwise occur secondary to compensatory renin release. Hypotension that occurs as a result of this mechanism can be corrected by volume expansion.

5.5 Impaired Renal Function

Monitor renal function periodically in patients treated with Lotrel. Changes in renal function, including acute renal failure, can be caused by drugs that affect the RAS. Patients whose renal function may depend in part on the activity of the RAS (e.g., patients with renal artery stenosis, severe heart failure, post-myocardial infarction or volume depletion) or who are on Nonsteroidal Anti-Inflammatory Drugs (NSAIDS) or ARBs may be at particular risk of developing acute renal failure on Lotrel. Consider withholding or discontinuing therapy in patients who develop a clinically significant decrease in renal function on Lotrel.

5.6 Hyperkalemia

Monitor serum potassium periodically in patients receiving Lotrel. Drugs that affect the RAS can cause hyperkalemia. Risk factors for the development of hyperkalemia include renal insufficiency, diabetes mellitus, and the concomitant use of potassium-sparing diuretics, potassium supplements, and/or potassium-containing salt substitutes. In U.S. placebo-controlled trials of Lotrel, hyperkalemia [serum potassium at least 0.5 mEq/L greater than the upper limit of normal (ULN)] not present at baseline occurred in approximately 1.5% of hypertensive patients receiving Lotrel. Increases in serum potassium were generally reversible.

5.7 Hepatitis and Hepatic Failure

There have been rare reports of predominantly cholestatic hepatitis and isolated cases of acute liver failure, some of them fatal, in patients on ACE inhibitors. The mechanism is not understood. Patients receiving ACE inhibitors who develop jaundice or marked elevation of hepatic enzymes should discontinue the ACE inhibitor and be kept under medical surveillance.

6 ADVERSE REACTIONS

6.1 Clinical Trials Experience

Because clinical trials are conducted under widely varying conditions, adverse reaction rates observed in the clinical trials of a drug cannot be directly compared to rates in the clinical trials of another drug and may not reflect the rates observed in practice. The adverse reaction information from clinical trials does, however, provide a basis for identifying the adverse events that appear to be related to drug use and for approximating rates.

Lotrel has been evaluated for safety in over 2,991 patients with hypertension; over 500 of these patients were treated for at least 6 months, and over 400 were treated for more than 1 year.

In a pooled analysis of 5 placebo-controlled trials involving Lotrel doses up to 5/20, the reported side effects were generally mild and transient, and there was no relationship between side effects and age, sex, race, or duration of therapy. Discontinuation of therapy due to side effects was required in approximately 4% of patients treated with Lotrel and in 3% of patients treated with placebo.

The most common reasons for discontinuation of therapy with Lotrel in these studies were cough and edema (including angioedema).

The peripheral edema associated with amlodipine use is dose-dependent. When benazepril is added to a regimen of amlodipine, the incidence of edema is substantially reduced.

The addition of benazepril to a regimen of amlodipine should not be expected to provide additional antihypertensive effect in African-Americans. However, all patient groups benefit from the reduction in amlodipine-induced edema.

The side effects considered possibly or probably related to study drug that occurred in these trials in more than 1% of patients treated with Lotrel are shown in the table below. Cough was the only adverse event with at least possible relationship to treatment that was more common on Lotrel (3.3%) than on placebo (0.2%).

Percent Incidence in U. S. Placebo-controlled Trials
 | Benazepril/Amlodipine | Benazepril | Amlodipine | Placebo
 | N = 760 | N = 554 | N = 475 | N = 408
Cough | 3.3 | 1.8 | 0.4 | 0.2
Headache | 2.2 | 3.8 | 2.9 | 5.6
Dizziness | 1.3 | 1.6 | 2.3 | 1.5
Edema* | 2.1 | 0.9 | 5.1 | 2.2
*Edema refers to all edema, such as dependent edema, angioedema, facial edema.

The incidence of edema was greater in patients treated with amlodipine monotherapy (5.1%) than in patients treated with Lotrel (2.1%) or placebo (2.2%).

Other side effects considered possibly or probably related to study drug that occurred in U.S. placebo-controlled trials of patients treated with Lotrel or in postmarketing experience were the following:

Body as a Whole: Asthenia and fatigue.

CNS: Insomnia, nervousness, anxiety, tremor, and decreased libido.

Dermatologic: Flushing, hot flashes, rash, skin nodule, and dermatitis.

Digestive: Dry mouth, nausea, abdominal pain, dyspepsia, and esophagitis.

Hematologic: Neutropenia

Musculoskeletal: cramps, and muscle cramps.

Urogenital: Sexual problems, such as impotence, and polyuria.

Monotherapies of benazepril and amlodipine have been evaluated for safety in clinical trials in over 6,000 and 11,000 patients, respectively. The observed adverse reactions to the monotherapies in these trials were similar to those seen in trials of Lotrel.

6.2 Postmarketing Experience

Because these reactions are reported voluntarily from a population of uncertain size, it is not always possible to reliably estimate their frequency or establish a causal relationship to drug exposure.

In postmarketing experience with benazepril, there have been rare reports of Stevens-Johnson syndrome, pancreatitis, hemolytic anemia, pemphigus, thrombocytopenia, paresthesia, dysgeusia, orthostatic symptoms and hypotension, angina pectoris and arrhythmia, pruritus, photosensitivity reaction, arthralgia, arthritis, myalgia, blood urea nitrogen (BUN) increase, serum creatinine increase, renal impairment, vision impairment, agranulocytosis, neutropenia.

Rare reports in association with use of amlodipine: gingival hyperplasia, tachycardia, jaundice, and hepatic enzyme elevations (mostly consistent with cholestasis severe enough to require hospitalization), leukocytopenia, allergic reaction, hyperglycemia, dysgeusia, hypoesthesia, paresthesia, syncope, peripheral neuropathy, hypertonia, visual impairment, diplopia, hypotension, vasculitis, rhinitis, gastritis, hyperhidrosis, pruritus, skin discoloration, urticaria, erythema multiform, muscle spasms, arthralgia, micturition disorder, nocturia, erectile dysfunction, malaise, weight decrease or gain.

Other potentially important adverse experiences attributed to other ACE inhibitors and calcium channel blockers include: eosinophilic pneumonitis (ACE inhibitors) and gynecomastia (CCBs).

7 DRUG INTERACTIONS

7.1 Drug/Drug Interactions

Amlodipine

Simvastatin: Coadministration of simvastatin with amlodipine increases the systemic exposure of simvastatin. Limit the dose of simvastatin in patients on amlodipine to 20 mg daily.

CYP3A4 Inhibitors: Coadministration with CYP3A inhibitors (moderate and strong) results in increased systemic exposure to amlodipine and may require dose reduction. Monitor for symptoms of hypotension and edema when amlodipine is coadministered with CYP3A4 inhibitors to determine the need for dose adjustment.

CYP3A4 Inducers: No information is available on the quantitative effects of CYP3A4 inducers on amlodipine. Blood pressure should be monitored when amlodipine is coadministered with CYP3A4 inducers (e.g. rifampicin, St. John’s Wort).

Benazepril

Potassium Supplements and Potassium-Sparing Diuretics: Benazepril can attenuate potassium loss caused by thiazide diuretics. Potassium-sparing diuretics (spironolactone, amiloride, triamterene, and others) or potassium supplements can increase the risk of hyperkalemia. If concomitant use of such agents is indicated, the patient’s serum potassium should be monitored frequently.

Lithium: Increased serum lithium levels and symptoms of lithium toxicity have been reported in patients receiving ACE inhibitors during therapy with lithium. When coadministering Lotrel and lithium, frequent monitoring of serum lithium levels is recommended.

Gold: Nitritoid reactions (symptoms include facial flushing, nausea, vomiting and hypotension) have been reported rarely in patients on therapy with injectable gold (sodium aurothiomalate) and concomitant ACE inhibitor therapy.

Nonsteroidal Anti-Inflammatory Drugs (NSAIDs) including Selective Cyclooxygenase-2 Inhibitors (COX-2 Inhibitors): In patients who are elderly, volume-depleted (including those on diuretic therapy), or with compromised renal function, coadministration of NSAIDs, including selective COX-2 inhibitors, with ACE inhibitors, including benazepril, may result in deterioration of renal function, including possible acute renal failure. These effects are usually reversible. Monitor renal function periodically in patients receiving benazepril and NSAID therapy.

The antihypertensive effect of ACE inhibitors, including benazepril, may be attenuated by NSAIDs.

Antidiabetic Agents: In rare cases, diabetic patients receiving an ACE inhibitor (including benazepril) concomitantly with insulin or oral antidiabetics may develop hypoglycemia. Such patients should therefore be advised about the possibility of hypoglycemic reactions and should be monitored accordingly.

Mammalian Target of Rapamycin (mTOR) Inhibitors: The risk of angioedema may be increased in patients receiving coadministration of ACE inhibitors and mTOR inhibitors (e.g., temsirolimus, sirolimus, everolimus).

Dual Blockade of the Renin-Angiotensin System (RAS): Dual blockade of the RAS with angiotensin receptor blockers, ACE inhibitors, or aliskiren is associated with increased risks of hypotension, hyperkalemia, and changes in renal function (including acute renal failure) compared to monotherapy. Most patients receiving the combination of two RAS inhibitors do not obtain any additional benefit compared to monotherapy. In general, avoid combined use of RAS inhibitors. Closely monitor blood pressure, renal function and electrolytes in patients on Lotrel and other agents that block the RAS.

Do not coadminister aliskiren with Lotrel in patients with diabetes. Avoid use of aliskiren with Lotrel in patients with renal impairment [glomerular filtration rate (GFR) < 60 mL/min].

Neprilysin Inhibitor: Patients taking concomitant neprilysin inhibitors may be at increased risk for angioedema [see Warnings and Precautions (5.1)].

8 USE IN SPECIFIC POPULATIONS

8.1 Pregnancy

Risk Summary

Lotrel can cause fetal harm when administered to a pregnant woman. Use of drugs that act on the RAS during the second and third trimesters of pregnancy reduces fetal renal function and increases fetal and neonatal morbidity and death. Most epidemiologic studies examining fetal abnormalities after exposure to antihypertensive use in the first trimester have not distinguished drugs affecting the RAS from other antihypertensive agents.

When pregnancy is detected, discontinue Lotrel as soon as possible.

The estimated background risk of major birth defects and miscarriage for the indicated population is unknown. All pregnancies have a background risk of birth defect, loss, or other adverse outcomes. In the U.S. general population, the estimated background risk of major birth defects and miscarriage in clinically recognized pregnancies is 2-4% and 15-20%, respectively.

Clinical Considerations

Disease-Associated Maternal and/or Embryo/Fetal Risk

Hypertension in pregnancy increases the maternal risk for pre-eclampsia, gestational diabetes, premature delivery, and delivery complications (e.g., need for cesarean section, and post-partum hemorrhage). Hypertension increases the fetal risk for intrauterine growth restriction and intrauterine death. Pregnant women with hypertension should be carefully monitored and managed accordingly.

Fetal/Neonatal Adverse Reactions

Oligohydramnios in pregnant women who use drugs affecting the renin-angiotensin system in the second and third trimesters of pregnancy can result in the following: reduced fetal renal function leading to anuria and renal failure, fetal lung hypoplasia, skeletal deformations, including skull hypoplasia, hypotension and death.

Perform serial ultrasound examinations to assess the intra-amniotic environment. Fetal testing may be appropriate, based on the week of gestation. Patients and physicians should be aware, however, that oligohydramnios may not appear until after the fetus has sustained irreversible injury. If oligohydramnios is observed, consider alternative drug treatment. Closely observe neonates with histories of in utero exposure to Lotrel for hypotension, oliguria, and hyperkalemia. In neonates with a history of in utero exposure to Lotrel, if oliguria or hypotension occurs, support blood pressure and renal perfusion. Exchange transfusions or dialysis may be required as a means of reversing hypotension and replacing renal function.

Data

Animal Data

Benazepril and Amlodipine:

When rats received benazepril:amlodipine at doses ranging from 5:2.5 to 50:25 mg/kg/day, dystocia was observed at an increasing dose-related incidence at all doses tested. On a body surface area basis, the 2.5 mg/kg/day dose of amlodipine is twice the amlodipine dose delivered when the maximum recommended dose of Lotrel is given to a 60 kg patient. Similarly, the 5 mg/kg/day dose of benazepril is approximately equivalent with the benazepril dose delivered when the maximum recommended dose of Lotrel is given to a 60 kg patient. No teratogenic effects were seen when benazepril and amlodipine were administered in combination to pregnant rats or rabbits. Rats received doses of up to 50:25 mg (benazepril:amlodipine)/kg/day (12 times the MRHD on a body surface area basis, assuming a 60 kg patient). Rabbits received doses of up to 1.5:0.75 mg/kg/day (equivalent to the maximum recommended dose of Lotrel given to a 60 kg patient).

8.2 Lactation

Risk Summary

Minimal amounts of unchanged benazepril and of benazeprilat are excreted into the breast milk of lactating women treated with benazepril, so that a newborn child ingesting nothing but breast milk would receive less than 0.1% of the maternal doses of benazepril and benazeprilat. Limited available data from a published clinical lactation study reports that amlodipine is present in human milk at an estimated median relative infant dose of 4.2%. No adverse effects of amlodipine on the breastfed infant have been observed. There is no available information on the effects of amlodipine or benazepril on milk production.

8.4 Pediatric Use

Safety and effectiveness in pediatric patients have not been established.

8.5 Geriatric Use

In geriatric patients, exposure to amlodipine is increased, thus consider lower initial doses of Lotrel [see Clinical Pharmacology (12.3)].

Of the total number of patients who received Lotrel in U.S. clinical studies of Lotrel, over 19% were 65 years or older while about 2% were 75 years or older. Overall differences in effectiveness or safety were not observed between these patients and younger patients. Clinical experience has not identified differences in responses between the elderly and younger patients, but greater sensitivity of some older individuals cannot be ruled out.

8.6 Hepatic Impairment

Exposure to amlodipine is increased in patients with hepatic insufficiency, thus consider using lower doses of Lotrel [see Clinical Pharmacology (12.3)].

8.7 Renal Impairment

In patients with severe renal impairment systemic exposure to benazepril is increased. The recommended dose of benazepril in this subgroup is 5 mg which is not an available strength with Lotrel. Lotrel is not recommended in patients with severe renal impairment. No dose adjustment of Lotrel is needed in patients with mild or moderate impairment of renal function [see Dosing and Administration (2.2), Warnings and Precautions (5.7) and Clinical Pharmacology (12.3)].

10 OVERDOSAGE

Only a few cases of human overdose with amlodipine have been reported. One patient was asymptomatic after a 250 mg ingestion; another, who combined 70 mg of amlodipine with an unknown large quantity of a benzodiazepine, developed refractory shock and died.

Human overdoses with any combination of amlodipine and benazepril have not been reported. In scattered reports of human overdoses with benazepril and other ACE inhibitors, there are no reports of death.

Treatment: Patients should be admitted to hospital and, generally, should be managed in an intensive care setting, with continuous monitoring of cardiac function, blood gases, and blood biochemistry. Emergency supportive measures such as artificial ventilation or cardiac pacing should be instituted if appropriate.

In the event of a potentially life-threatening oral overdose, use induction of vomiting or gastric lavage and/or activated charcoal to remove the drug from the gastrointestinal tract (only if presented within 1 hour after ingestion of Lotrel).

Other clinical manifestations of overdose should be managed symptomatically based on modern methods of intensive care.

To obtain up-to-date information about the treatment of overdose, a good resource is your certified Regional Poison-Control Center. Telephone numbers of certified poison-control centers are listed in the Physicians’ Desk Reference (PDR). In managing overdose, consider the possibilities of multiple-drug overdoses, drug-drug interactions, and unusual drug kinetics in your patient.

The most likely effect of overdose with Lotrel is vasodilation, with consequent hypotension and tachycardia. Simple repletion of central fluid volume (Trendelenburg positioning, infusion of crystalloids) may be sufficient therapy, but pressor agents (norepinephrine or high-dose dopamine) may be required. With abrupt return of peripheral vascular tone, overdoses of other dihydropyridine calcium channel blockers have sometimes progressed to pulmonary edema, and patients must be monitored for this complication.

Analyses of bodily fluids for concentrations of amlodipine, benazepril, or their metabolites are not widely available. Such analyses are, in any event, not known to be of value in therapy or prognosis.

No data are available to suggest physiologic maneuvers (e.g., maneuvers to change the pH of the urine) that might accelerate elimination of amlodipine, benazepril, or their metabolites. Benazeprilat is only slightly dialyzable; attempted clearance of amlodipine by hemodialysis or hemo-perfusion has not been reported, but amlodipine’s high protein binding makes it unlikely that these interventions will be of value.

Angiotensin II could presumably serve as a specific antagonist-antidote to benazepril, but angiotensin II is essentially unavailable outside of scattered research laboratories.

11 DESCRIPTION

Lotrel is a combination of amlodipine besylate and benazepril hydrochloride.

Benazepril hydrochloride is a white to off-white crystalline powder, soluble (greater than 100 mg/mL) in water, in ethanol, and in methanol. Benazepril hydrochloride’s chemical name is 3-[[1-(ethoxycarbonyl)-3-phenyl-(1S)-propyl]amino]-2,3,4,5-tetrahydro-2-oxo-1H-1-(3S)-benzazepine-1-acetic acid monohydrochloride; its structural formula is:

Its empirical formula is C24H28N2O5•HCl, and its molecular weight is 460.96.

Benazeprilat, the active metabolite of benazepril, is a nonsulfhydryl ACE inhibitor. Benazepril is converted to benazeprilat by hepatic cleavage of the ester group.

Amlodipine besylate is a white to pale yellow crystalline powder, slightly soluble in water and sparingly soluble in ethanol. Its chemical name is (R,S)3-ethyl-5-methyl-2-(2-aminoethoxymethyl)-4-(2-chlorophenyl)-1,4-dihydro-6-methyl-3,5-pyridinedicarboxylate benzenesulfonate; its structural formula is:

Its empirical formula is C20H25ClN2O5•C6H6O3S, and its molecular weight is 567.1.

Amlodipine besylate is the besylate salt of amlodipine, a dihydropyridine calcium channel blocker.

Lotrel is available as capsules containing amlodipine besylate (6.9 mg or 13.9 mg, equivalent to 5 mg or 10 mg of amlodipine respectively), with 10 mg, 20 mg, or 40 mg of benazepril hydrochloride providing for the following available combinations: 5/10 mg, 5/20 mg, 10/20 mg, and 10/40 mg.

The inactive ingredients of the capsules are calcium phosphate, cellulose compounds, colloidal silicon dioxide, crospovidone, gelatin, hydrogenated castor oil (not present in 10/40 mg strength), iron oxides, lactose monohydrate, magnesium stearate, polysorbate 80, silicon dioxide, sodium lauryl sulfate, sodium starch (potato) glycolate, starch (corn), talc, and titanium dioxide.

12 CLINICAL PHARMACOLOGY

12.1 Mechanism of Action

Benazepril

Benazepril and benazeprilat inhibit ACE in human subjects and in animals. ACE is a peptidyl dipeptidase that catalyzes the conversion of angiotensin I to the vasoconstrictor substance angiotensin II. Angiotensin II also stimulates aldosterone secretion by the adrenal cortex.

Inhibition of ACE results in decreased plasma angiotensin II, which leads to decreased vasopressor activity and to decreased aldosterone secretion. The latter decrease may result in a small increase of serum potassium. Hypertensive patients treated with benazepril and amlodipine for up to 56 weeks had elevations of serum potassium up to 0.2 mEq/L [see Warnings and Precautions (5.6)].

Removal of angiotensin II negative feedback on renin secretion leads to increased plasma renin activity. In animal studies, benazepril had no inhibitory effect on the vasopressor response to angiotensin II and did not interfere with the hemodynamic effects of the autonomic neurotransmitters acetylcholine, epinephrine, and norepinephrine.

ACE is identical to kininase, an enzyme that degrades bradykinin. Whether increased levels of bradykinin, a potent vasodepressor peptide, play a role in the therapeutic effects of Lotrel remains to be elucidated.

While the mechanism through which benazepril lowers blood pressure is believed to be primarily suppression of the renin-angiotensin aldosterone system, benazepril has an antihypertensive effect even in patients with low-renin hypertension.

Amlodipine

Amlodipine is a dihydropyridine calcium antagonist (calcium ion antagonist or slow channel blocker) that inhibits the transmembrane influx of calcium ions into vascular smooth muscle and cardiac muscle. Experimental data suggest that amlodipine binds to both dihydropyridine and nondihydropyridine binding sites. The contractile processes of cardiac muscle and vascular smooth muscle are dependent upon the movement of extracellular calcium ions into these cells through specific ion channels. Amlodipine inhibits calcium ion influx across cell membranes selectively, with a greater effect on vascular smooth muscle cells than on cardiac muscle cells. Negative inotropic effects can be detected in vitro but such effects have not been seen in intact animals at therapeutic doses. Serum calcium concentration is not affected by amlodipine. Within the physiologic pH range, amlodipine is an ionized compound (pKa = 8.6), and its kinetic interaction with the calcium channel receptor is characterized by a gradual rate of association and dissociation with the receptor binding site, resulting in a gradual onset of effect.

Amlodipine is a peripheral arterial vasodilator that acts directly on vascular smooth muscle to cause a reduction in peripheral vascular resistance and reduction in blood pressure.

12.2 Pharmacodynamics

Benazepril

Single and multiple doses of 10 mg or more of benazepril cause inhibition of plasma ACE activity by at least 80% to 90% for at least 24 hours after dosing. For up to 4 hours after a 10 mg dose, pressor responses to exogenous angiotensin I were inhibited by 60% to 90%.

Administration of benazepril to patients with mild-to-moderate hypertension results in a reduction of both supine and standing blood pressure to about the same extent, with no compensatory tachycardia. Symptomatic postural hypotension is infrequent, although it can occur in patients who are salt and/or volume depleted [see Warnings and Precautions (5.4)].

The antihypertensive effects of benazepril were not appreciably different in patients receiving high- or low-sodium diets.

In normal human volunteers, single doses of benazepril caused an increase in renal blood flow but had no effect on glomerular filtration rate.

Amlodipine

Following administration of therapeutic doses to patients with hypertension, amlodipine produces vasodilation resulting in a reduction of supine and standing blood pressures. These decreases in blood pressure are not accompanied by a significant change in heart rate or plasma catecholamine levels with chronic dosing.

With chronic once-daily administration, antihypertensive effectiveness is maintained for at least 24 hours. Plasma concentrations correlate with effect in both young and elderly patients. The magnitude of reduction in blood pressure with amlodipine is also correlated with the height of pretreatment elevation; thus, individuals with moderate hypertension (diastolic pressure 105–114 mmHg) had about 50% greater response than patients with mild hypertension (diastolic pressure 90–104 mmHg). Normotensive subjects experienced no clinically significant change in blood pressure (+1/-2 mmHg).

In hypertensive patients with normal renal function, therapeutic doses of amlodipine resulted in a decrease in renal vascular resistance and an increase in glomerular filtration rate and effective renal plasma flow without change in filtration fraction or proteinuria.

As with other calcium channel blockers, hemodynamic measurements of cardiac function at rest and during exercise (or pacing) in patients with normal ventricular function treated with amlodipine have generally demonstrated a small increase in cardiac index without significant influence on dP/dt or on left ventricular end diastolic pressure or volume. In hemodynamic studies, amlodipine has not been associated with a negative inotropic effect when administered in the therapeutic dose range to intact animals and humans, even when coadministered with beta blockers to humans.

Amlodipine does not change sinoatrial (SA) nodal function or atrioventricular (AV) conduction in intact animals or humans. In clinical studies in which amlodipine was administered in combination with beta blockers to patients with either hypertension or angina, no adverse effects on electrocardiographic parameters were observed.

Amlodipine has demonstrated beneficial clinical effects in patients with chronic stable angina, vasospastic angina and angiographically documented coronary artery disease.

12.3 Pharmacokinetics

The rate and extent of absorption of benazepril and amlodipine from Lotrel are the same as when administered as individual tablets. Absorption from the individual tablets is not influenced by the presence of food in the gastrointestinal tract; food effects on absorption from Lotrel have not been studied.

Absorption: Following oral administration of Lotrel, peak plasma concentrations of amlodipine are reached in 6 to 12 hours. Absolute bioavailability has been calculated as between 64% and 90%. Following oral administration of Lotrel, the peak plasma concentrations of benazepril are reached in 0.5 to 2 hours. The cleavage of the ester group (primarily in the liver) converts benazepril to its active metabolite, benazeprilat, which reaches peak plasma concentrations in 1.5 to 4 hours. The extent of absorption of benazepril is at least 37%. Amlodipine and benazepril exhibit dose proportional pharmacokinetics between the therapeutic dose range of 2.5 and 10 mg and 10 and 20 mg, respectively.

Distribution: The apparent volume of distribution of amlodipine is about 21 L/kg. In vitro studies indicate that approximately 93% of circulating amlodipine is bound to plasma proteins in hypertensive patients. The apparent volume of distribution of benazeprilat is about 0.7 L/kg. Approximately 93% of circulating amlodipine is bound to plasma proteins, and the bound fraction of benazeprilat is slightly higher. On the basis of in vitro studies, benazeprilat’s degree of protein binding should be unaffected by age, by hepatic dysfunction, or—over the therapeutic concentration range—by concentration.

Metabolism: Amlodipine is extensively (approximately 90%) metabolized in the liver to inactive metabolites. Benazepril is extensively metabolized to form benazeprilat as the main metabolite, which occurs by enzymatic hydrolysis, mainly in the liver. Two minor metabolites are the acyl glucuronide conjugates of benazepril and benazeprilat.

Elimination: Amlodipine elimination from plasma is biphasic with a terminal elimination half-life of approximately 30 to 50 hours. Steady-state plasma levels are reached after once-daily dosing for 7 to 8 days. Ten percent of unchanged drug and 60% of amlodipine metabolites are excreted in urine. Effective elimination half-life of amlodipine is 2 days. Benazepril is eliminated mainly by metabolic clearance. Benazeprilat is eliminated via the kidneys and the bile; renal excretion is the main route in patients with normal renal function. In the urine, benazepril accounts for less than 1 % and benazeprilat for about 20% of an oral dose. Elimination of benazeprilat is biphasic with an initial half-life of about 3 hours and a terminal half-life of about 22 hours. Benazeprilat’s effective elimination half-life is 10 to 11 hours, while that of amlodipine is about 2 days, so steady-state levels of the 2 components are achieved after about a week of once-daily dosing.

Specific Populations

Geriatric Patients: No specific clinical studies were performed to understand the impact of age on the pharmacokinetics of amlodipine and benazepril as fixed dose combination. As individual component amlodipine is extensively metabolized in the liver. In the elderly, clearance of amlodipine is decreased with resulting increases in peak plasma levels, elimination half-life and area-under-the-plasma-concentration curve [see Use in Specific Populations (8.5)].

Hepatic Impairment: Patients with hepatic insufficiency have decreased clearance of amlodipine with a resulting increase in AUC of approximately 40 to 60%. Pharmacokinetics of benazepril is not significantly influenced by hepatic impairment [see Use in Specific Populations (8.6)].

Renal Impairment: The disposition of benazepril and benazeprilat in patients with mild-to-moderate renal insufficiency (CrCl greater than 30 mL/min) is similar to that in patients with normal renal function. In patients with CrCl less than or equal to 30 mL/min, peak benazeprilat levels and the effective half-life increase, resulting in higher systemic exposures. Pharmacokinetics of amlodipine is not significantly influenced by renal impairment [see Dosage and Administration (2.2), Use in Specific Populations (8.7) and Warnings and Precautions (5.7)].

Drug Interactions

Amlodipine

In vitro data in human plasma indicate that amlodipine has no effect on the protein binding of digoxin, phenytoin, warfarin, and indomethacin.

Cimetidine: Coadministration of amlodipine with cimetidine did not alter the pharmacokinetics of amlodipine.

Grapefruit juice: Coadministration of 240 mL of grapefruit juice with a single oral dose of amlodipine 10 mg in 20 healthy volunteers had no significant effect on the pharmacokinetics of amlodipine.

Maalox® (antacid): Coadministration of the antacid Maalox with a single dose of amlodipine had no significant effect on the pharmacokinetics of amlodipine.

Sildenafil: A single 100 mg dose of sildenafil in subjects with essential hypertension had no effect on the pharmacokinetic parameters of amlodipine. When amlodipine and sildenafil were used in combination, each agent independently exerted its own blood pressure lowering effect.

Atorvastatin: Coadministration of multiple 10 mg doses of amlodipine with 80 mg of atorvastatin resulted in no significant change in the steady-state pharmacokinetic parameters of atorvastatin.

Digoxin: Coadministration of amlodipine with digoxin did not change serum digoxin levels or digoxin renal clearance in normal volunteers.

Ethanol (alcohol): Single and multiple 10 mg doses of amlodipine had no significant effect on the pharmacokinetics of ethanol.

Warfarin: Coadministration of amlodipine with warfarin did not change the warfarin prothrombin response time.

Simvastatin: Coadministration of multiple doses of 10 mg of amlodipine with 80 mg simvastatin resulted in a 77% increase in exposure to simvastatin compared to simvastatin alone.

CYP3A Inhibitors: Coadministration of a 180 mg daily dose of diltiazem with 5 mg amlodipine in elderly hypertensive patients resulted in a 60% increase in amlodipine systemic exposure. Erythromycin coadministration in healthy volunteers did not significantly change amlodipine systemic exposure. However, strong inhibitors of CYP3A4 (e.g., ketoconazole, itraconazole, ritonavir) may increase the plasma concentrations of amlodipine to a greater extent.

Benazepril

The pharmacokinetic properties of benazepril are not affected by hydrochlorothiazide, furosemide, chlorthalidone, digoxin, propranolol, atenolol, nifedipine, amlodipine, naproxen, acetylsalicylic acid, or cimetidine. Likewise the administration of benazepril does not substantially affect the pharmacokinetics of these medications.

13 NONCLINICAL TOXICOLOGY

13.1 Carcinogenesis, Mutagenesis, Impairment of Fertility

Carcinogenicity and mutagenicity studies have not been conducted with this combination. However, these studies have been conducted with amlodipine and benazepril alone (see below). No adverse effects on fertility occurred when the benazepril:amlodipine combination was given orally to rats of either sex at doses up to 15:7.5 mg (benazepril:amlodipine)/kg/day, prior to mating and throughout gestation.

Benazepril: No evidence of carcinogenicity was found when benazepril was administered to rats and mice for up to 2 years at doses of up to 150 mg/kg/day. When compared on the basis of body surface area, this dose is 18 and 9 times (rats and mice, respectively) the maximum recommended human dose (MRHD) (calculations assume a patient weight of 60 kg). No mutagenic activity was detected in the Ames test in bacteria, in an in vitro test for forward mutations in cultured mammalian cells, or in a nucleus anomaly test. At doses of 50 to 500 mg/kg/day (6 to 60 times the MRHD on a body surface area basis), benazepril had no adverse effect on the reproductive performance of male and female rats.

Amlodipine: Rats and mice treated with amlodipine maleate in the diet for up to 2 years, at concentrations calculated to provide daily dosage levels of 0.5, 1.25, and 2.5 mg amlodipine/kg/day, showed no evidence of a carcinogenic effect of the drug. For the mouse, the highest dose was, on a body surface area basis, similar to the MRHD of 10 mg amlodipine/day. For the rat, the highest dose was, on a body surface area basis, about two and a half times the MRHD (Calculations based on a 60 kg patient). Mutagenicity studies conducted with amlodipine maleate revealed no drug-related effects at either the gene or chromosome level. There was no effect on the fertility of rats treated orally with amlodipine maleate (males for 64 days and females for 14 days prior to mating) at doses of up to 10 mg amlodipine/kg/day (about 10 times the MRHD of 10 mg/day on a body surface area basis).

14 CLINICAL STUDIES

Over 950 patients received Lotrel once-daily in 6 double-blind, placebo-controlled studies. The antihypertensive effect of a single dose persisted for 24 hours, with peak reductions achieved 2 to 8 hours after dosing.

Once-daily doses of benazepril/amlodipine using benazepril doses of 10 to 20 mg and amlodipine doses of 2.5 to 10 mg decreased seated pressure (systolic/diastolic) 24 hours after dosing by about 10–25/6–13 mmHg.

In 2 studies in patients not adequately controlled on either benazepril 40 mg alone (n = 329) or amlodipine 10 mg alone (n = 812) once-daily doses of Lotrel 10/40 mg further decreased seated blood pressure compared to the respective monotherapy alone.

Combination therapy was effective in blacks and nonblacks. Both components contributed to the antihypertensive efficacy in nonblacks, but virtually all of the antihypertensive effect in blacks could be attributed to the amlodipine component. Among nonblack patients in placebo-controlled trials comparing Lotrel to the individual components, the blood pressure lowering effects of the combination were shown to be additive and in some cases synergistic.

During chronic therapy with Lotrel, the maximum reduction in blood pressure with any given dose is generally achieved after 1 to 2 weeks. The antihypertensive effects of Lotrel have continued during therapy for at least 1 year. Abrupt withdrawal of Lotrel has not been associated with a rapid increase in blood pressure.

16 HOW SUPPLIED/STORAGE AND HANDLING

Lotrel is available as capsules containing amlodipine besylate (6.9 mg or 13.9 mg, equivalent to 5 mg or 10 mg of amlodipine respectively), with 10 mg, 20 mg, or 40 mg of benazepril hydrochloride providing for the following available combinations: 5/10 mg, 5/20 mg, 10/20 mg, and 10/40 mg. All strengths are packaged in bottles of 100 capsules.

Capsules are imprinted with “Lotrel” and appropriate code.

Dose | Capsule Color/Code | NDC Code
 |  | Bottle of 100
5/10 mg | light brown with 2 white bands/2260 | NDC 0078-0405-05
5/20 mg | pink with 2 white bands/2265 | NDC 0078-0406-05
10/20 mg | purple (amethyst) with 2 white bands/0364 | NDC 0078-0364-05
10/40 mg | dark blue with 2 white bands/0379 | NDC 0078-0379-05

Storage: Store at 20°C to 25°C (68°F to 77°F); excursions permitted between 15°C to 30°C (59°F to 86°F). [See USP controlled room temperature]. Protect from moisture. Dispense in tight container (USP).

17 PATIENT COUNSELING INFORMATION

Advise the patient to read the FDA-approved patient labeling (Patient Information).

Pregnancy: Advise female patients of childbearing age about the consequences of exposure to Lotrel during pregnancy. Discuss treatment options with women planning to become pregnant. Ask patients to report pregnancies to their physicians as soon as possible [see Warnings and Precautions (5.1) and Use in Specific Populations (8.1)].

Symptomatic Hypotension: Advise patients that lightheadedness can occur, especially during the first days of therapy, and that it should be reported to their healthcare provider. Tell patients that if syncope occurs to discontinue Lotrel until the physician has been consulted. Caution all patients that inadequate fluid intake, excessive perspiration, diarrhea, or vomiting can lead to an excessive fall in blood pressure, with the same consequences of lightheadedness and possible syncope [see Warnings and Precautions (5.4)].

Hyperkalemia: Advise patients not to use salt substitutes without consulting their healthcare provider [see Drug Interactions (7)].

T2021-38

Patient Information

LOTREL® (low-TREL)

(amlodipine and benazepril hydrochloride)

capsules

Read this Patient Information leaflet before you start taking LOTREL and each time you get a refill. There may be new information. This leaflet does not replace talking with your doctor. If you have any questions, ask your doctor or pharmacist.

What is the most important information I should know about LOTREL?
1. LOTREL can cause harm or death to an unborn baby.
2. Talk to your doctor about other ways to lower your blood pressure if you plan to become pregnant.
3. If you get pregnant while taking LOTREL, tell your doctor right away.

What is LOTREL?

LOTREL contains 2 prescription medicines that work together to lower blood pressure: amlodipine besylate, a calcium channel blocker, and benazepril hydrochloride, an ACE inhibitor. Your doctor will prescribe LOTREL only after other medicines haven’t worked.

High Blood Pressure (hypertension). Blood pressure is the force of blood in your blood vessels. You have high blood pressure when the force is too much. LOTREL can help your blood vessels relax so your blood pressure is lower.

LOTREL has not been studied in children.

Who should not take LOTREL?

Don’t take LOTREL if you are allergic to any of the ingredients. There is a complete list at the end of this leaflet.

What should I tell my Doctor before taking LOTREL?

Tell your doctor about all your medical conditions, including if:

- you are pregnant or plan to become pregnant. See “What is the most important information I should know about LOTREL?”
- you are breastfeeding. LOTREL is present in human milk. It is not known whether LOTREL affects your breastfed baby or milk production.
- you have a heart condition
- you have liver problems
- you have kidney problems
- you are about to have an operation (including dental surgery) or emergency treatment
- you are suffering from several episodes of vomiting or diarrhea
- you are treated for hyperkalemia (too much potassium in the blood)

Keep a list of your medicines with you, including vitamins and natural or herbal remedies, to show your doctor or pharmacist. Some of your other medicines and LOTREL could affect each other, causing serious side effects. Tell your doctor about all your medicines, especially:

- Simvastatin (a medicine used to control elevated cholesterol)
- medicines for high blood pressure or heart failure
- water pills, extra potassium or a salt substitute
- Lithium
- potassium-containing medicines, potassium supplements or salt substitutes containing potassium
- cyclosporine, an immunosuppressant medicine used in transplanted patients to reduce the risk of organ rejection
- indomethacin and other nonsteroidal anti-inflammatory drugs (NSAIDs), medicines used to relieve pain and inflammation
- insulin or oral antidiabetics, medicines that help a person with diabetes to control their level of glucose (sugar) in the blood
- gold for the treatment of rheumatoid arthritis
- probenecid, a medicine used to treat gout and hyperuricemia
- medicines used to prevent and treat fungal skin infections (e.g., ketoconazole, itraconazole)
- medicines used to treat AIDS or HIV infections (e.g., ritonavir, indinavir)
- medicines used to treat bacterial infections (e.g., clarithromycin)
- medicines used in organ transplant recipients or for treating some cancers (e.g. temsirolimus, sirolimus, everolimus)

Avoid alcohol until you have discussed the matter with your doctor. Alcohol may make blood pressure fall more and/or increase the possibility of dizziness or fainting.

How do I take LOTREL?

1. Take LOTREL exactly as your doctor tells you.
2. Take LOTREL at the same time each day, with or without food.
3. If you miss a dose, take it as soon as you remember. If it is more than 12 hours, just take your next dose at the regular time.
4. Your doctor may test for kidney problems or check your blood potassium level.
5. If you take too much LOTREL, call your doctor or Poison Control Center, or go to the emergency room.
6. Tell all your doctors or dentist you are taking LOTREL if you:
  - are going to have surgery
  - are getting allergy shots for bee stings
  - go for kidney dialysis

What are the possible side effects of LOTREL?

LOTREL can cause serious side effects including:

- serious allergic reactions that can be life threatening.
  Stop LOTREL and get emergency help right away if you get:
  - swelling of your face, eyelids, lips, tongue or throat
  - have trouble swallowing
  - asthma (wheezing) or other breathing problems
  These allergic reactions are rare but happen more times in people who are African-American.
- low blood pressure (hypotension). Low blood pressure is most likely to happen if you also take water pills, are on a low salt diet, get dialysis treatments, have heart problems or get sick with vomiting or diarrhea. Lie down if you feel faint or dizzy.
- liver problems. Call your doctor if:
  - you have nausea
  - you feel more tired or weaker than usual
  - you have itching
  - your skin or eyes look yellow
  - you have pain in your upper right stomach
  - you have flu-like symptoms
1. kidney problems. Some people will have changes on blood tests for kidney function and need a lower dose of LOTREL. Call your doctor if you get swelling in your feet, ankles, or hands or unexplained weight gain.
2. more chest pain and heart attacks in people that already have severe heart problems. Get emergency help if you get worse chest pain or chest pain that does not go away.

The more common side effects of LOTREL are:

- dizziness, fainting on standing up
- cough (dry, nonproductive, mainly at night, continuing)
- swelling of the feet, ankles, and hands

If any of these affects you severely, tell your doctor.

These are not all the side effects of LOTREL. For a complete list, ask your doctor or pharmacist.

How do I store LOTREL?

1. Store LOTREL at room temperature between 59°F to 86°F (15°C to 30°C).
2. Keep LOTREL in a closed container in a dry place.
3. Keep LOTREL and all medicines out of the reach of children.

General Information about LOTREL

Doctors can also use medicine for a condition that is not in the patient information leaflet. Take LOTREL the way your doctor tells you. Do not share it with other people. It may harm them.

For more information, ask your doctor or pharmacist, visit www.LOTREL.com on the Internet, or call 1-888-669-6682.

What are the ingredients in LOTREL?

Active ingredients: amlodipine besylate (the active ingredient found in Norvasc®), benazepril hydrochloride (Lotensin®)

Inactive ingredients: calcium phosphate, cellulose compounds, colloidal silicon dioxide, crospovidone, gelatin, hydrogenated castor oil (not present in 10/40 mg strength), iron oxides, lactose monohydrate, magnesium stearate, polysorbate 80, silicon dioxide, sodium lauryl sulfate, sodium starch (potato) glycolate, starch (corn), talc, and titanium dioxide.

Distributed by:
Novartis Pharmaceuticals Corporation
East Hanover, New Jersey 07936

© Novartis

T2021-39
April 2021

PRINCIPAL DISPLAY PANEL

NDC 0078-0405-05

Lotrel® 5 mg */10 mg

amlodipine and benazepril
hydrochloride capsules

*each capsule contains 6.9 mg of
amlodipine besylate

100 capsules

Rx only

NOVARTIS

PRINCIPAL DISPLAY PANEL

NDC 0078-0406-05

Lotrel® 5 mg*/20 mg

amlodipine and benazepril
hydrochloride capsules

*each capsule contains 6.9 mg of
amlodipine besylate

100 capsules

Rx only

NOVARTIS

PRINCIPAL DISPLAY PANEL

NDC 0078-0364-05

Lotrel® 10 mg*/20 mg

amlodipine and benazepril
hydrochloride capsules

*each capsule contains 13.9 mg of
amlodipine besylate

100 capsules

Rx only

NOVARTIS

PRINCIPAL DISPLAY PANEL

NDC 0078-0379-05

Lotrel® 10 mg*/40 mg

amlodipine and benazepril
hydrochloride capsules

*each capsule contains 13.9 mg of
amlodipine besylate

100 capsules

Rx only

NOVARTIS